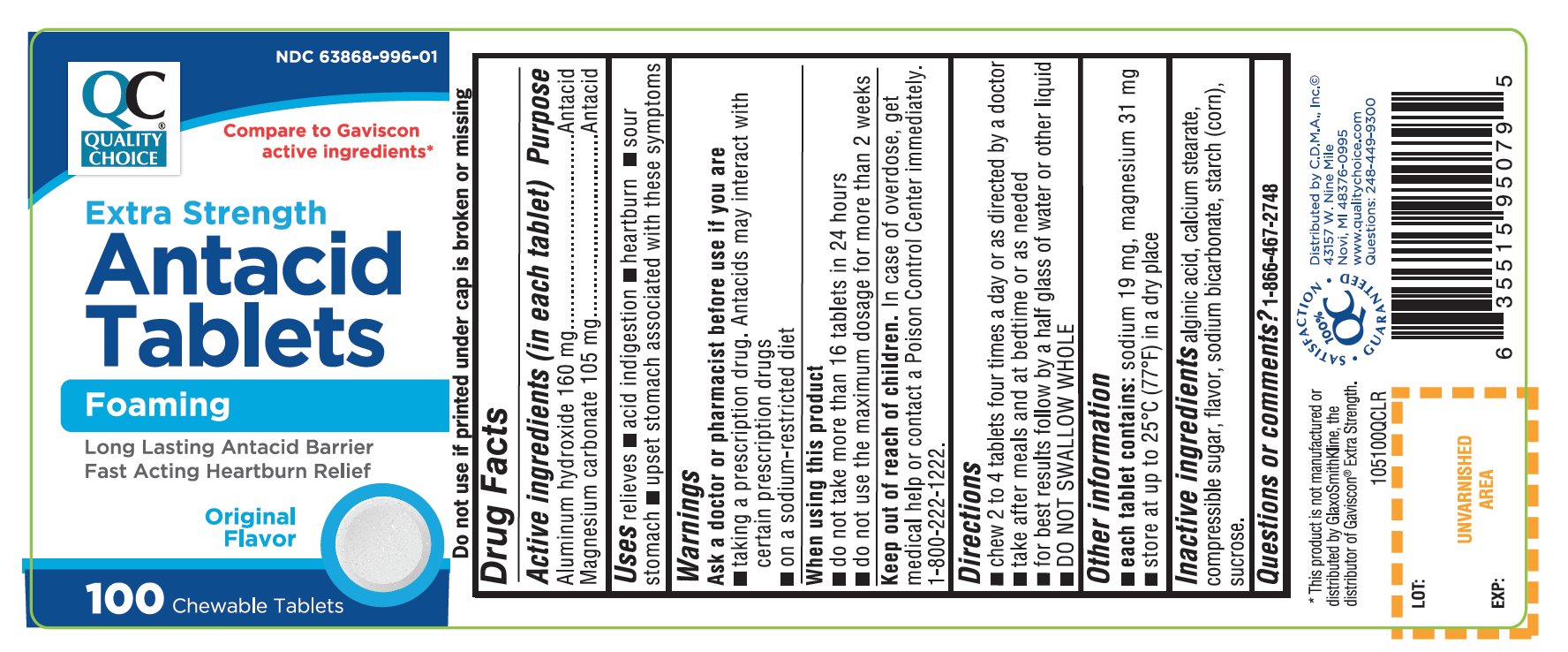 DRUG LABEL: Extra Strength Antacid

NDC: 63868-996 | Form: TABLET, CHEWABLE
Manufacturer: CHAIN DRUG MARKETING ASSOCIATION INC.
Category: otc | Type: HUMAN OTC DRUG LABEL
Date: 20251203

ACTIVE INGREDIENTS: ALUMINUM HYDROXIDE 160 mg/1 1; MAGNESIUM CARBONATE 105 mg/1 1
INACTIVE INGREDIENTS: ALGINIC ACID; CALCIUM STEARATE; CORN SYRUP; SODIUM BICARBONATE; STARCH, CORN; SUCROSE

Quality Choice Antacid Tablets Extra Strength Original Flavor

Active ingredients (in each tablet)

Aluminum hydroxide 160 mg

Magnesium carbonate 105 mg

Purpose

Antacid

Antacid

Uses

relieves

- acid indigestion
- heartburn
- sour stomach
- upset stomach associated with these symptoms

Warnings

Ask a doctor or pharmacist before use if you are

- taking a prescription drug. Antacids may interact with certain prescription drugs
- on a sodium-restricted diet

When using this product

- do not take more than 16 tablets in 24 hours
- do not use the maximum dosage for more than 2 weeks

Keep out of reach of children.

In case of overdose, get medical help or contact a Poison Control Center immediately.

1-800-222-1222

Directions

- chew 2 to 4 tablets four times a day or as directed by a doctor
- take after meals and at bedtime or as needed
- for best results follow by a half glass of water or other liquid
- DO NOT SWALLOW WHOLE

Other information

- each tablet contains:sodium 19 mg, magnesium 31 mg.
- Store at up to 25°C (77°F) in a dry place.

Inactive ingredients

alginic acid, calcium stearate, compressible sugar, flavor, sodium bicarbonate, starch (corn), sucrose.

Questions or comments

1-866-467-2748

Principal Display Panel

QUALITY CHOICE®

NDC 63868-996-01

Compare To Gaviscon® active ingredients*

Extra Strength

Antacid Tablets

Foaming

Long Lasting Antacid Barrier

Fast Acting Heartburn Relief

Original Flavor

100% QC SATISFACTION GUARANTEED

- DO NOT USE IF PRINTED INNER SEAL UNDER CAP IS BROKEN OR MISSING.
- Distributed by C.D.M.A., Inc.©
- 43157 W. Nine Mile
- Novi, MI 48376-0995
- www.qualitychoice.com
- Questions: 248-449-9300

*This product is not manufactured or distributed by GlaxoSmithKline, the distributor of Gaviscon®Extra Strength.